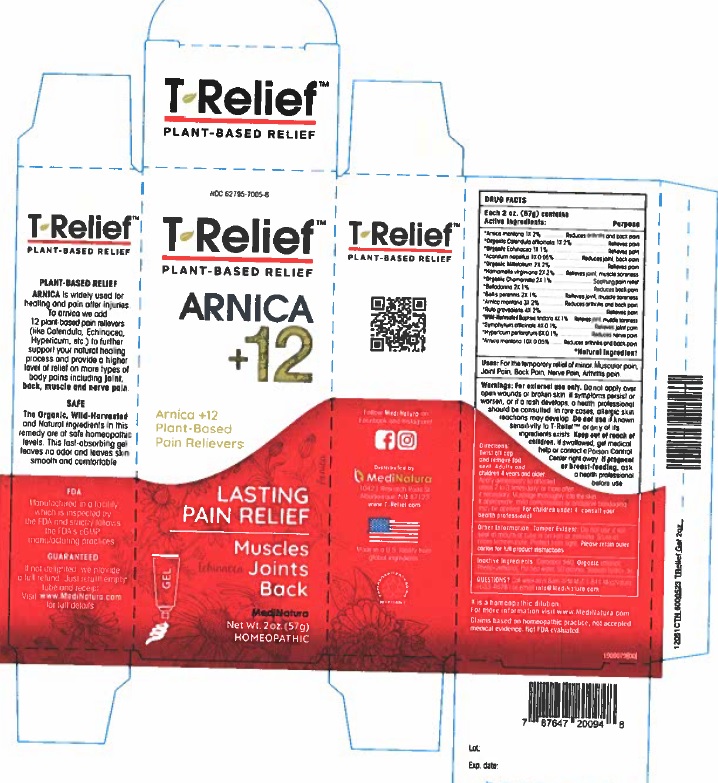 DRUG LABEL: T-Relief
NDC: 62795-7005 | Form: GEL
Manufacturer: MediNatura Inc
Category: homeopathic | Type: HUMAN OTC DRUG LABEL
Date: 20230927

ACTIVE INGREDIENTS: ACONITUM NAPELLUS 1 [hp_X]/1 g; ARNICA MONTANA 1 [hp_X]/1 g; BAPTISIA TINCTORIA ROOT 4 [hp_X]/1 g; ATROPA BELLADONNA 2 [hp_X]/1 g; BELLIS PERENNIS 2 [hp_X]/1 g; CALENDULA OFFICINALIS FLOWERING TOP 1 [hp_X]/1 g; MATRICARIA RECUTITA 2 [hp_X]/1 g; ECHINACEA, UNSPECIFIED 1 [hp_X]/1 g; HAMAMELIS VIRGINIANA ROOT BARK/STEM BARK 2 [hp_X]/1 g; HYPERICUM PERFORATUM 6 [hp_X]/1 g; ACHILLEA MILLEFOLIUM 2 [hp_X]/1 g; RUTA GRAVEOLENS FLOWERING TOP 2 [hp_X]/1 g; COMFREY ROOT 4 [hp_X]/1 g
INACTIVE INGREDIENTS: CARBOMER HOMOPOLYMER TYPE C (ALLYL PENTAERYTHRITOL CROSSLINKED); PHENOXYETHANOL; WATER; ALCOHOL; SODIUM HYDROXIDE

T-Relief Gel

ACTIVE INGREDIENTS

Active ingredients Purpose

*Aconitum napellus 1X 0.5%................Reduces joint and back pain

*Arnica montana 1X 2%........Reduces joint and back pain

*Arnica montana 3X 2%..........Reduces joint and back pain

*Arnica montana10X 2%........Reduces joint and back pain

*Baptisia tinctoria 4X 1% ..................Reduces joint and muscle pain

*Belladonna 2X 1%...........................Reduces back pain

*Bellis perennis 2X 1%......................Relieves joint and muscle soreness

*Calendula officinalis 1X 1%..............Relieves pain

*Chamomilla 2X 1%.........................Soothing pain relief

*Echinacea 1X 1%............................Relieves pain

*Hamamelis virginiana 2X 2%...........Relieves joint and muscle soreness

*Hypericum perforatum 6X 0.1%.........Relieves pain

*Millefolium 2X 2%...........................Relieves pain

*Ruta graveolens 4X 2%..................Relieves pain

*Symphytum officinale 4X 0.1%..........Relieves joint pain

*Natural Ingredients

USES

For the temporary relief of minor: Joint Pain • Back Pain • Muscular Pain • Nerve Pain

KEEP OUT OF REACH OF CHILDREN

INDICATIONS

Relieves

• Joint Pain

• Back Pain

•Muscular Pain

•Nerve Pain

WARNINGS

For external use only. Do not apply over open wounds or broken skin. If symptoms persist or worsen, or if a rash develops, a health professional should be consulted. In rare cases, allergic skin reactions may develop. Do not use if known sensitivity to T-ReliefTM or any of its ingredients exists.

Keep out of reach of children. If swallowed, get medical help or contact a Poison Control Center right away. If pregnant or breast-feeding, ask a health professional before use.

DIRECTIONS

Twist off cap and remove the foil seal.

Adults and children 4 years and older: Apply generously to affected areas 2 to 3 times daily, or more often if necessary. Massage thoroughly into the skin. If appropriate, mild compression or occlusive bandaging may be applied.

For children under 4,consult your health professional.

INACTIVE INGREDIENTS

Carbomer 980, Phenoxyethanol, Purified Water, SD Alcohol 3C, Sodium Hydroxide.